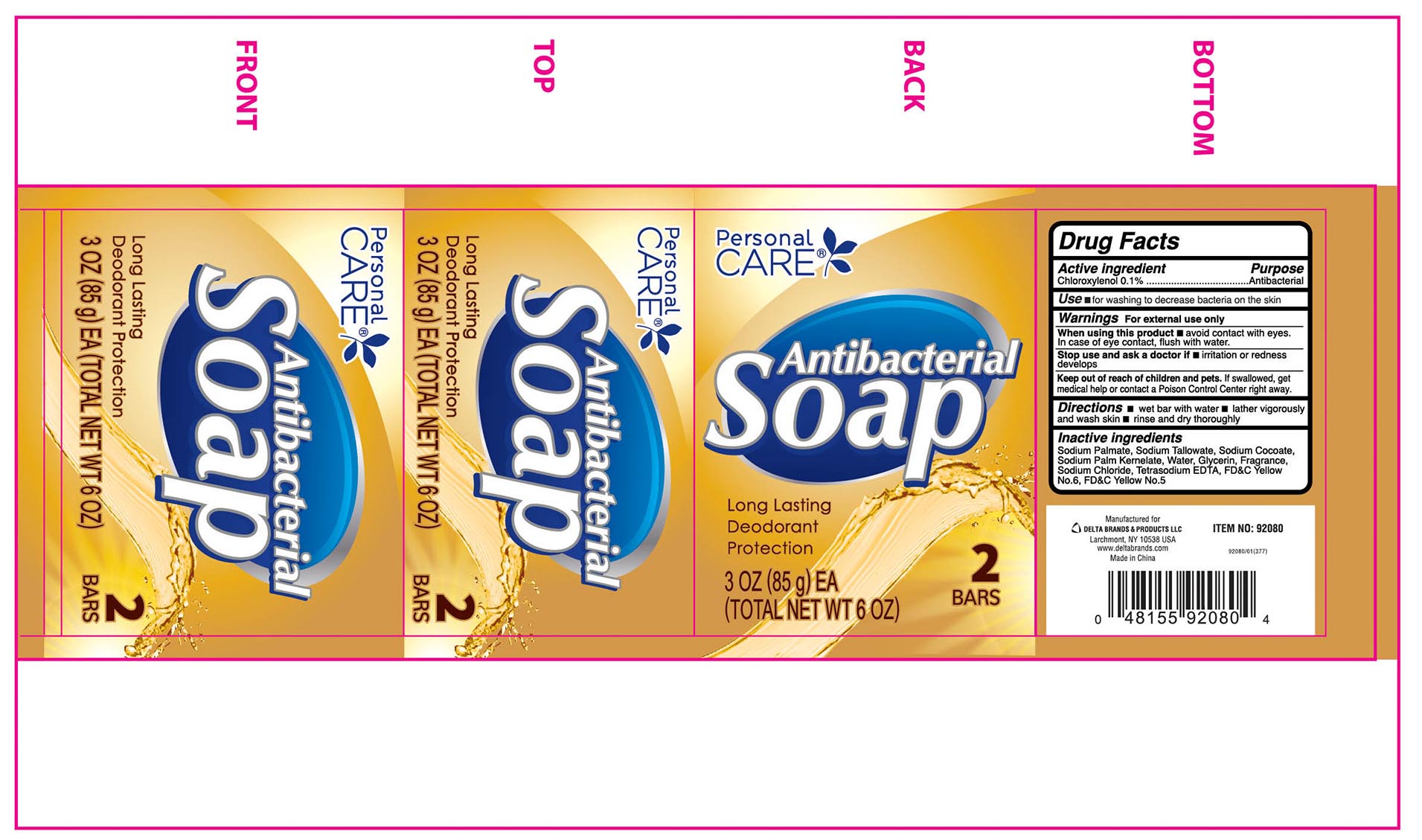 DRUG LABEL: Personal CARE
NDC: 72133-048 | Form: SOAP
Manufacturer: Delta Brands & Products LLC
Category: otc | Type: HUMAN OTC DRUG LABEL
Date: 20180406

ACTIVE INGREDIENTS: CHLOROXYLENOL 0.1 g/100 g
INACTIVE INGREDIENTS: SODIUM TALLOWATE, BEEF; SODIUM COCOATE; SODIUM PALM KERNELATE; SODIUM PALMITATE; WATER; GLYCERIN; SODIUM CHLORIDE; EDETATE SODIUM; FD&C YELLOW NO. 5; FD&C YELLOW NO. 6

Drug Facts

Active ingredient

Chloroxylenol 0.1%

Purpose

Antibacterial

Use

■for hand washing to decrease bacteria on the skin

Warnings

For external use only

When using this product

■avoid contact with eyes. In case of eye contact, flush with water

Stop use and ask a doctor if

■irritation and redness develops

Keep out of reach of children

If swallowed, get medical help or contact a Poison Control Center right away.

Directions

■ wet bar with water ■ lather vigorously and wash skin ■ rinse and dry thoroughly

Inactive ingredients

Sodium Palmate, Sodium Tallowate, Sodium Cocoate, Sodium Palm Kernelate, Water, Glycerin, Fragrance,Sodium Chloride, Tetrasodium EDTA, FD&C Yellow No. 6, FD&C Yellow No. 5